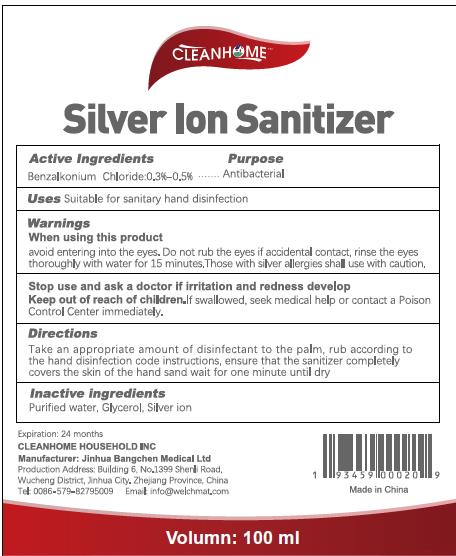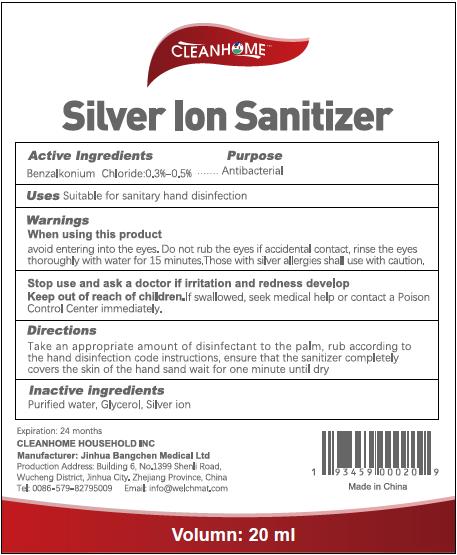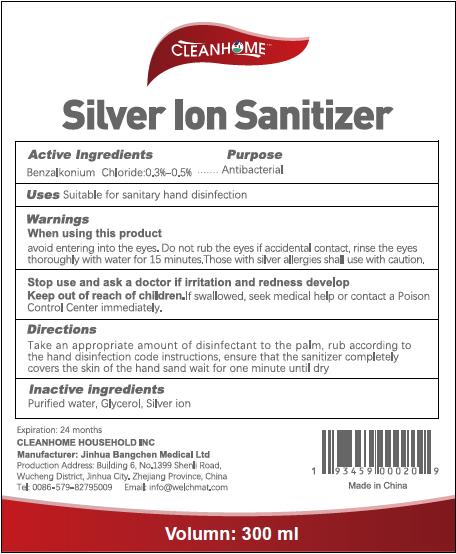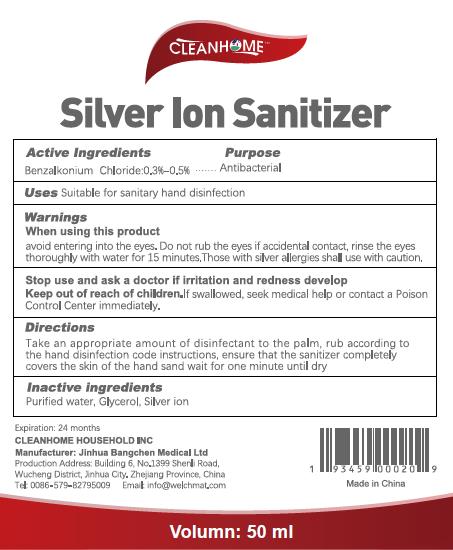 DRUG LABEL: Hand sanitizer
NDC: 81452-001 | Form: SPRAY
Manufacturer: CLEANHOME HOUSEHOLD
Category: otc | Type: HUMAN OTC DRUG LABEL
Date: 20210121

ACTIVE INGREDIENTS: BENZALKONIUM CHLORIDE 0.3 g/100 mL
INACTIVE INGREDIENTS: WATER; SILVER CHLORIDE; GLYCERIN

cleanhome 0.13% BENZALKONIUM CHLORIDE

Active Ingredient

Benzalkonium Chloride 0.3%-0.5%

Purpose

Antibacterial

Inactive ingredients

Purified water, Glycerol, Silver Ion

Directions

Take an appropriate amount of disinfectant to the palm, rub according to the hand disinfection code instructions, ensure that the sanitizer completely covers the skin of the hand sand wait for one minute until dry

USE

Suitable for sanitary hand disinfection.

Warning

When using this product, avoid entering into the eyes.

Do not rub the eyes if accidental contact, rinse the eyes thoroughly with water for 15 minutes.

Those with silver allergies shall use with caution.

Keep out of reach of children.

If swallowed, seek medical help or contact a Poison Control Center immediately.

PACKAGE LABEL

20 ml NDC 81452-001-04

50ml NDC 81452-001-03

100ml NDC 81452-001-02

300ml NDC 81452-001-01